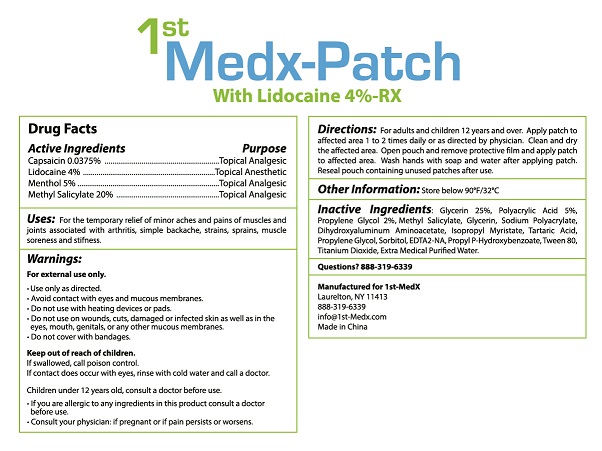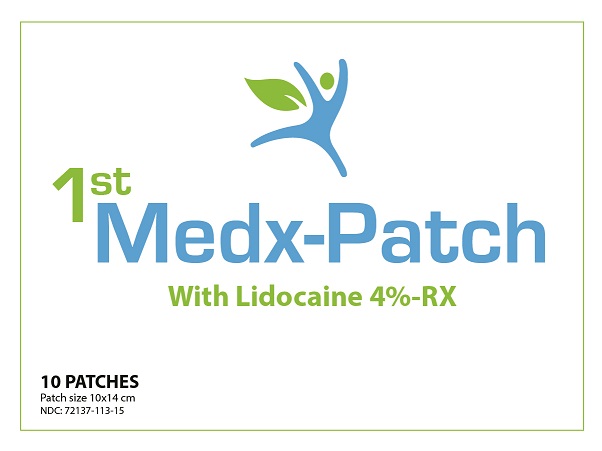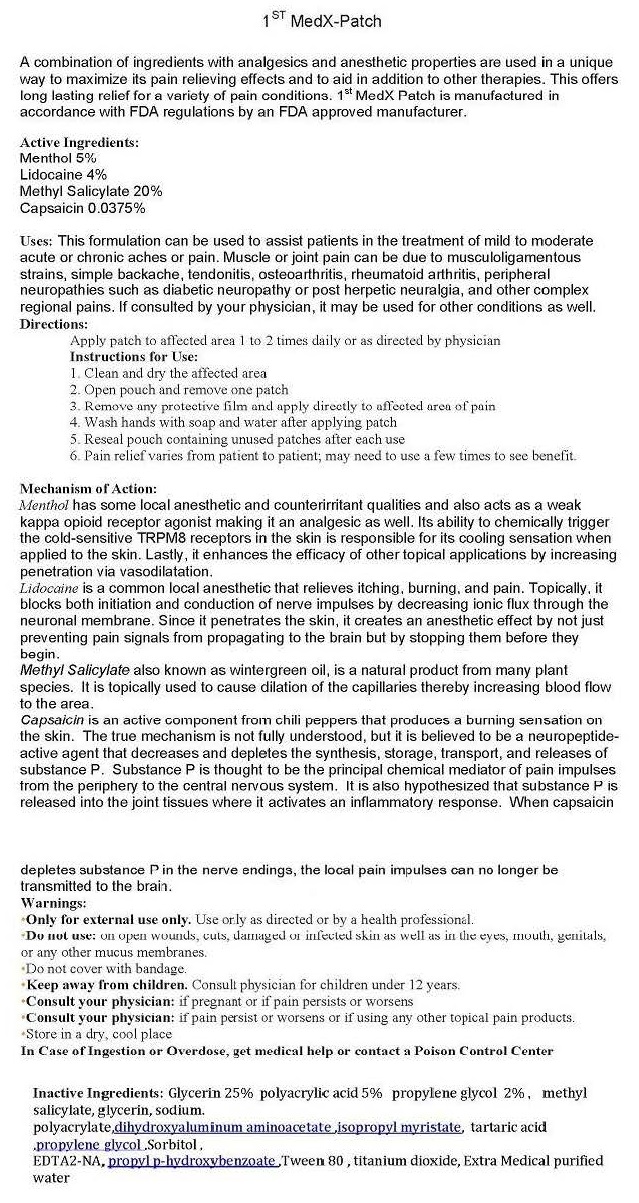 DRUG LABEL: 1ST MEDXPATCH
NDC: 72137-113 | Form: PATCH
Manufacturer: 1ST MEDX LLC
Category: prescription | Type: HUMAN PRESCRIPTION DRUG LABEL
Date: 20260108

ACTIVE INGREDIENTS: CAPSAICIN 0.0375 g/1 1; LIDOCAINE 4 g/1 1; MENTHOL 5 g/1 1; METHYL SALICYLATE 20 g/1 1
INACTIVE INGREDIENTS: GLYCERIN; POLYACRYLIC ACID (450000 MW); PROPYLENE GLYCOL; SODIUM POLYACRYLATE (2500000 MW); DIHYDROXYALUMINUM AMINOACETATE; ISOPROPYL MYRISTATE; TARTARIC ACID; SORBITOL; EDETATE DISODIUM; PROPYLPARABEN; POLYSORBATE 80; TITANIUM DIOXIDE; WATER

1ST MEDX (as PLD) - PATCH WITH LIDOCAINE 4%-RX (72137-113) - DELIST

ACTIVE INGREDIENTS:

CAPSAICIN O.O375%

LIDOCAINE 4%

MENTHOL 5%

METHYL SALICYLATE 20%

USES:

FOR THE TEMPORARY RELIEF OF MINOR ACHES AND PAINS OF MUSCLES AND JOINTS ASSOCIATED WITH ARTHRITIS, SIMPLE BACKACHE, STRAINS, SPRAINS, MUSCLE SORENESS AND STIFFNESS.

WARNINGS:

FOR EXTERNAL USE ONLY.

- USE ONLY AS DIRECTED.
- AVOID CONTACT WITH EYES AND MUCOUS MEMBRANES.
- DO NOT USE ON WOUNDS, CUTS, DAMAGED OR INFECTED SKIN AS WELL AS IN THE EYES, MOUTH, GENITALS, OR ANY OTHER MUCOUS MEMBRANES.
- DO NOT COVER WITH BANDAGES.

KEEP OUT OF REACH OF CHILDREN.

IF SWALLOWED, CALL POISON CONTROL

WARNINGS AND PRECAUTIONS

IF CONTACT DOES OCCUE WITH EYES, RINSE WITH COLD WATER AND CALL A DOCTOR.

CHILDREN UNDER 12 YEARS OLD, CONSULT A DOCTOR BEFORE USE.

- IF YOU ARE ALLERGIC TO ANY INGREDIENTS IN THIS PRODUCT CONSULT A DOCTOR BEFORE USE.
- CONSULT YOUR PHYSICIAN: IF PREGNANT OR IF PAIN PERSISTS OR WORSENS.

DIRECTIONS:

FOR ADULTS AND CHILDREN 12 YEARS AND OVER. APPLY PATCH TO AFFECTED AREA 1 TO 2 TIMES DAILY OR AS DIRECTED BY PHYSICIAN. CLEAN AND DRY THE AFFECTED AREA. WASH HANDS WITH SOAP AND WATER AFTER APPLYING PATCH. RESEAL POUCH CONTAINING UNUSED PATCHES AFTER USE.

OTHER INFORMATION:

STORE BELOW 90°F/32°C

INACTIVE INGREDIENTS:

GLYCERIN 25%, POLYACRYLIC ACID 5%, PROPYLENE GLYCOL 2%, METHYL SALICYLATE, GLYCERIN, SODIUM POLYACRYLATE, DIHYDROXYALUMINUM AMINOACETATE, ISOPROPYL MYRISTATE, TARTARIC ACID, PROPYLENE GLYCOL, SORBITOL, EDTA2-NA, PROPYL P-HYDROXYBENZOATE, TWEEN 80, TITANIUM DIOXIDE, EXTRA MEDICAL PURIFIED WATER.

QUESTIONS?

888-319-6339